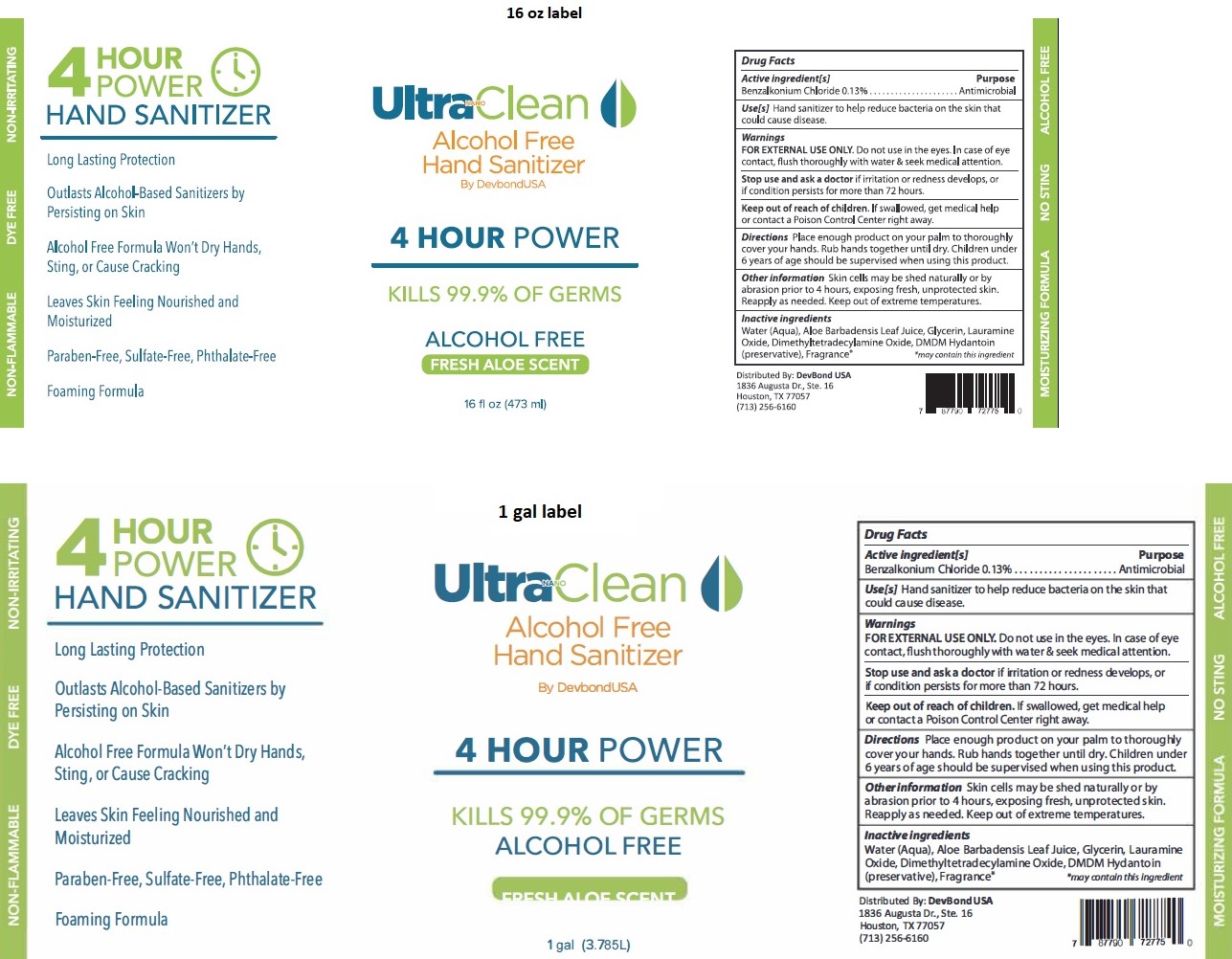 DRUG LABEL: Ultra NANO Clean Alcohol Free Hand Sanitizer 4 HOUR POWER
NDC: 79993-440 | Form: LIQUID
Manufacturer: Devbond Consulting, L.L.C.
Category: otc | Type: HUMAN OTC DRUG LABEL
Date: 20220127

ACTIVE INGREDIENTS: BENZALKONIUM CHLORIDE 0.13 g/100 mL
INACTIVE INGREDIENTS: WATER; ALOE VERA LEAF; GLYCERIN; LAURAMINE OXIDE; MYRISTAMINE OXIDE; DMDM HYDANTOIN

Ultra NANO Clean Alcohol Free Hand Sanitizer 4 HOUR POWER

Active ingredient[s]

Benzalkonium Chloride 0.13%

Purpose

Antimicrobial

Use[s]

Hand sanitizer to help reduce bacteria on the skin that could cause disease.

Warnings

FOR EXTERNAL USE ONLY. Do not use in the eyes. In case of eye contact, flush thoroughly with water & seek medical attention.

Stop use and ask a doctor if irritation or redness develops, or if condition persists for more than 72 hours.

Keep out of reach of children. If swallowed, get medical help or contact a Poison Control Center right away.

Directions

Place enough product on your palm to thoroughly cover your hands. Rub hands together until dry. Children under 6 years of age should be supervised when using this product.

Other information

Skin cells may be shed naturally or by abrasion prior to 4 hours, exposing fresh, unprotected skin. Reapply as needed. Keep out of extreme temperatures.

Inactive ingredients

Water (Aqua), Aloe Barbadensis Leaf Juice, Glycerin, Lauramine Oxide, Dimethyltetradecylamine Oxide, DMDM Hydantoin (preservative), Fragrance*
*may contain this ingredient

KILLS 99.9% OF GERMS

FRESH ALOE SCENT

NON-FLAMMABLE

DYE FREE

NON-IRRITATING

MOISTURIZING FORMULA

NO-STING

Long Lasting Protection

Outlasts Alcohol-Based Sanitizers by Persisting on Skin

Alcohol Free Formula Won't Dry Hands, Sting, or Cause Cracking

Leaves Skin Feeling Nourished and Moisturized

Paraben-Free, Sulfate-Free, Phthalate-Free

Foaming Formula

Distributed By: DevBond USA

1836 Augusta Dr., Ste. 16

Houston, TX 77057

(713) 256-6160